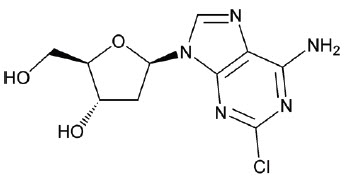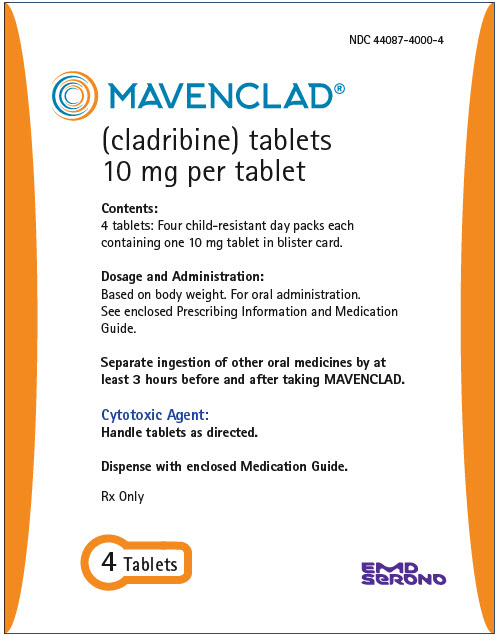 DRUG LABEL: Mavenclad
NDC: 44087-4000 | Form: TABLET
Manufacturer: EMD Serono, Inc.
Category: prescription | Type: HUMAN PRESCRIPTION DRUG LABEL
Date: 20250905

ACTIVE INGREDIENTS: Cladribine 10 mg/1 1
INACTIVE INGREDIENTS: Sorbitol 64.04 mg/1 1; Magnesium stearate; HYDROXYPROPYL BETADEX

HIGHLIGHTS OF PRESCRIBING INFORMATION

These highlights do not include all the information needed to use MAVENCLAD safely and effectively. See full prescribing information for MAVENCLAD.
MAVENCLAD® (cladribine) tablets, for oral use
Initial U.S. Approval: 1993

WARNING: MALIGNANCIES AND RISK OF TERATOGENICITY

See full prescribing information for complete boxed warning.

- Malignancies

MAVENCLAD may increase the risk of malignancy. MAVENCLAD is contraindicated in patients with current malignancy; evaluate the benefits and risks on an individual basis for patients with prior or increased risk of malignancy. (5.1)

- Risk of Teratogenicity

MAVENCLAD is contraindicated for use in pregnant women and in women and men of reproductive potential who do not plan to use effective contraception because of the risk of fetal harm. (5.2)

RECENT MAJOR CHANGES

Dosage and Administration (2.1) | 5/2024
Warnings and Precautions (5.4, 5.7) | 5/2024

1 INDICATIONS AND USAGE

MAVENCLAD is a purine antimetabolite indicated for the treatment of relapsing forms of multiple sclerosis (MS), to include relapsing-remitting disease and active secondary progressive disease, in adults. Because of its safety profile, use of MAVENCLAD is generally recommended for patients who have had an inadequate response to, or are unable to tolerate, an alternate drug indicated for the treatment of MS. (1, 5)

Limitations of Use

MAVENCLAD is not recommended for use in patients with clinically isolated syndrome (CIS) because of its safety profile. (1, 5)

2 DOSAGE AND ADMINISTRATION

- Assessments are required prior to starting each MAVENCLAD treatment course. (2.1)
- Cumulative dosage of 3.5 mg/kg administered orally and divided into 2 treatment courses (1.75 mg/kg per treatment course). Each treatment course is divided into 2 treatment cycles. (2.2)
- MAVENCLAD is a cytotoxic drug. (2.4)
- Separate administration from any other oral drug by at least 3 hours. (2.4)

3 DOSAGE FORMS AND STRENGTHS

Tablets: 10 mg (3)

4 CONTRAINDICATIONS

- Patients with current malignancy. (4)
- Pregnant women, and women and men of reproductive potential who do not plan to use effective contraception during MAVENCLAD dosing and for 6 months after the last dose in each treatment course. (4, 8.3)
- HIV infection. (4)
- Active chronic infections (e.g., hepatitis or tuberculosis). (4)
- History of hypersensitivity to cladribine. (4, 5.8)
- Women intending to breastfeed on a MAVENCLAD treatment day and for 10 days after the last dose. (4, 8.2)

5 WARNINGS AND PRECAUTIONS

- Lymphopenia: Monitor lymphocyte counts before, during and after treatment. (5.3)
- Infections: Serious, including life-threatening and fatal infections, have occurred. Screen patients for active and latent infections; delay treatment until infection is fully resolved or controlled. Vaccination of patients seronegative to varicella zoster virus (VZV) is recommended prior to treatment. Vaccination of patients seropositive to VZV with zoster vaccine recombinant, adjuvanted, is recommended prior to or during treatment. Administer anti-herpes prophylaxis in patients with lymphocyte counts less than 200 cells per microliter. Monitor for infections. (5.4)
- Hematologic toxicity: Monitor complete blood count before, during and after treatment. (5.5)
- Graft-versus-host-disease with blood transfusion: Irradiation of cellular blood components is recommended. (5.6)
- Liver injury: Clinically significant liver injury has occurred. Obtain tests prior to treatment. Discontinue if clinicallysignificant injury is suspected. (5.7)

6 ADVERSE REACTIONS

Most common adverse reactions (incidence > 20%) are upper respiratory tract infection, headache, and lymphopenia. (6.1)

To report SUSPECTED ADVERSE REACTIONS, contact EMD Serono at 1-800-283-8088 ext. 5563 or FDA at 1-800-FDA-1088 or www.fda.gov/medwatch.

7 DRUG INTERACTIONS

- Immunosuppressive drugs: Consider overlapping effects on immune system, when used sequentially. Concomitant use not recommended. (7.1)
- Hematotoxic drugs: Monitor patients for additive effects on the hematological profile. (7.3)
- Antiviral and antiretroviral drugs: Avoid concomitant use. (7.4)
- BCRP or ENT/CNT inhibitors: May alter bioavailability of cladribine. Avoid concomitant use. (7.5)

FULL PRESCRIBING INFORMATION

WARNING: MALIGNANCIES AND RISK OF TERATOGENICITY

- Malignancies

Treatment with MAVENCLAD may increase the risk of malignancy. MAVENCLAD is contraindicated in patients with current malignancy. In patients with prior malignancy or with increased risk of malignancy, evaluate the benefits and risks of the use of MAVENCLAD on an individual patient basis. Follow standard cancer screening guidelines in patients treated with MAVENCLAD [see Contraindications (4) and Warnings and Precautions (5.1)].

- Risk of Teratogenicity

MAVENCLAD is contraindicated for use in pregnant women and in women and men of reproductive potential who do not plan to use effective contraception because of the potential for fetal harm. Malformations and embryolethality occurred in animals. Exclude pregnancy before the start of treatment with MAVENCLAD in females of reproductive potential. Advise females and males of reproductive potential to use effective contraception during MAVENCLAD dosing and for 6 months after the last dose in each treatment course. Stop MAVENCLAD if the patient becomes pregnant [see Contraindications (4), Warnings and Precautions (5.2), and Use in Specific Populations (8.1, 8.3)].

1 INDICATIONS AND USAGE

MAVENCLAD is indicated for the treatment of relapsing forms of multiple sclerosis (MS), to include relapsing-remitting disease and active secondary progressive disease, in adults. Because of its safety profile, use of MAVENCLAD is generally recommended for patients who have had an inadequate response to, or are unable to tolerate, an alternate drug indicated for the treatment of MS [see Warnings and Precautions (5)].

Limitations of Use

MAVENCLAD is not recommended for use in patients with clinically isolated syndrome (CIS) because of its safety profile [see Warnings and Precautions (5)].

2 DOSAGE AND ADMINISTRATION

2.1 Assessments Prior to Starting Each MAVENCLAD Treatment Course

Cancer Screening

Follow standard cancer screening guidelines because of the risk of malignancies [see Boxed Warning and Warnings and Precautions (5.1)].

Pregnancy

Exclude pregnancy prior to treatment with MAVENCLAD in females of reproductive potential [see Contraindications (4), Warnings and Precautions (5.2), and Use in Specific Populations (8.1, 8.3)].

Complete Blood Count (CBC)

Obtain a CBC with differential including lymphocyte count [see Dosage and Administration (2.5) and Warnings and Precautions (5.3)]. Lymphocytes must be:

- within normal limits before initiating the first treatment course
- at least 800 cells per microliter before initiating the second treatment course

If necessary, delay the second treatment course for up to 6 months to allow for recovery of lymphocytes to at least 800 cells per microliter. If this recovery takes more than 6 months, the patient should not receive further treatment with MAVENCLAD.

Infections [see Warnings and Precautions (5.4)]

- Exclude HIV infection.
- Perform tuberculosis screening.
- Screen for hepatitis B and C.
- Evaluate for acute infection. Consider a delay in MAVENCLAD treatment until any acute infection is fully controlled.
- Vaccination of patients who are seronegative for VZV is recommended prior to initiation of MAVENCLAD.
- Vaccination of patients who are seropositive to VZV is recommended with zoster vaccine recombinant, adjuvanted. Patients may be administered zoster vaccine recombinant, adjuvanted at any time prior to or during the year 1 or year 2 course of MAVENCLAD treatment. These patients may also be administered the vaccine if their lymphocyte counts are ≤ 500 cells per microliter.
- Administer all immunizations (except as noted for VZV) according to immunization guidelines prior to starting MAVENCLAD. Administer live-attenuated or live vaccines at least 4 to 6 weeks prior to starting MAVENCLAD.
- Obtain a baseline (within 3 months) magnetic resonance imaging prior to the first treatment course because of the risk of progressive multifocal leukoencephalopathy (PML).

Liver Injury

Obtain serum aminotransferase, alkaline phosphatase, and total bilirubin levels prior to each treatment cycle and course [see Warnings and Precautions (5.7)].

2.2 Recommended Dosage

The recommended cumulative dosage of MAVENCLAD is 3.5 mg per kg body weight administered orally and divided into 2 yearly treatment courses (1.75 mg per kg per treatment course) (see Table 1). Each treatment course is divided into 2 treatment cycles:

Administration of First Treatment Course

- First Course/First Cycle: start any time.
- First Course/Second Cycle: administer 23 to 27 days after the last dose of First Course/First Cycle.

Administration of Second Treatment Course

- Second Course/First Cycle: administer at least 43 weeks after the last dose of First Course/Second Cycle.
- Second Course/Second Cycle: administer 23 to 27 days after the last dose of Second Course/First Cycle.

Table 1 Dose of MAVENCLAD per Cycle by Patient Weight in Each Treatment Course
Weight Range | Dose in mg (Number of 10 mg Tablets) per Cycle
kg | First Cycle | Second Cycle
40 [The use of MAVENCLAD in patients weighing less than 40 kg has not been investigated.] to less than 50 | 40 mg (4 tablets) | 40 mg (4 tablets)
50 to less than 60 | 50 mg (5 tablets) | 50 mg (5 tablets)
60 to less than 70 | 60 mg (6 tablets) | 60 mg (6 tablets)
70 to less than 80 | 70 mg (7 tablets) | 70 mg (7 tablets)
80 to less than 90 | 80 mg (8 tablets) | 70 mg (7 tablets)
90 to less than 100 | 90 mg (9 tablets) | 80 mg (8 tablets)
100 to less than 110 | 100 mg (10 tablets) | 90 mg (9 tablets)
110 and above | 100 mg (10 tablets) | 100 mg (10 tablets)

Administer the cycle dosage as 1 or 2 tablets once daily over 4 or 5 consecutive days [see How Supplied/Storage and Handling (16.1)]. Do not administer more than 2 tablets daily.

Following the administration of 2 treatment courses, do not administer additional MAVENCLAD treatment during the next 2 years. Treatment during these 2 years may further increase the risk of malignancy [see Warnings and Precautions (5.1)]. The safety and efficacy of reinitiating MAVENCLAD more than 2 years after completing 2 treatment courses has not been studied.

2.3 Missed Dose

If a dose is missed, patients should not take double or extra doses.

If a dose is not taken on the scheduled day, then the patient must take the missed dose on the following day and extend the number of days in that treatment cycle. If two consecutive doses are missed, the treatment cycle is extended by 2 days.

2.4 Administration

MAVENCLAD tablets are taken orally, with water, and swallowed whole without chewing. MAVENCLAD can be taken with or without food.

Separate administration of MAVENCLAD and any other oral drugs by at least 3 hours during the 4 to 5 day MAVENCLAD treatment cycles [see Clinical Pharmacology (12.6)].

MAVENCLAD is a cytotoxic drug. Follow applicable special handling and disposal procedures [see References (15)]. MAVENCLAD is an uncoated tablet and must be swallowed immediately once removed from the blister. If a tablet is left on a surface, or if a broken or fragmented tablet is released from the blister, the area must be thoroughly washed with water.

The patient's hands must be dry when handling the tablets and washed thoroughly afterwards. Avoid prolonged contact with skin.

2.5 Laboratory Testing and Monitoring to Assess Safety

Cancer Screening

Follow standard cancer screening guidelines in patients treated with MAVENCLAD [see Dosage and Administration (2.1) and Warnings and Precautions (5.1)].

Complete Blood Count

Obtain complete blood count (CBC) with differential including lymphocyte count:

- before initiating the first treatment course of MAVENCLAD
- before initiating the second treatment course of MAVENCLAD
- 2 and 6 months after start of treatment in each treatment course; if the lymphocyte count at month 2 is below 200 cells per microliter, monitor monthly until month 6. See Warnings and Precautions (5.3, 5.4) for instructions based on the patient's lymphocyte counts and clinical status (e.g., infections). Hold MAVENCLAD therapy if the lymphocyte count is below 200 cells per microliter
- periodically thereafter and when clinically indicated [see Warnings and Precautions (5.5)]

2.6 Recommended Concomitant Medication

Herpes Prophylaxis

Administer anti-herpes prophylaxis in patients with lymphocyte counts less than 200 cells per microliter [see Warnings and Precautions (5.4)].

3 DOSAGE FORMS AND STRENGTHS

MAVENCLAD is available as 10 mg tablets. The tablets are uncoated, white, round, biconvex, and engraved with a "C" on one side and "10" on the other side.

4 CONTRAINDICATIONS

MAVENCLAD is contraindicated:

- in patients with current malignancy [see Warnings and Precautions (5.1)].
- in pregnant women and in women and men of reproductive potential who do not plan to use effective contraception during MAVENCLAD dosing and for 6 months after the last dose in each treatment course. May cause fetal harm [see Warnings and Precautions (5.2) and Use in Specific Populations (8.1, 8.3)].
- in patients infected with the human immunodeficiency virus (HIV) [see Warnings and Precautions (5.4)].
- in patients with active chronic infections (e.g., hepatitis or tuberculosis) [see Warnings and Precautions (5.4)].
- in patients with a history of hypersensitivity to cladribine [see Warnings and Precautions (5.8)].
- in women intending to breastfeed on a MAVENCLAD treatment day and for 10 days after the last dose [see Use in Specific Populations (8.2)].

5 WARNINGS AND PRECAUTIONS

5.1 Malignancies

Treatment with MAVENCLAD may increase the risk of malignancy. In controlled and extension clinical studies worldwide, malignancies occurred more frequently in MAVENCLAD-treated patients [10 events in 3,754 patient-years (0.27 events per 100 patient-years)], compared to placebo patients [3 events in 2,275 patient-years (0.13 events per 100 patient-years)]. Malignancy cases in MAVENCLAD patients included metastatic pancreatic carcinoma, malignant melanoma (2 cases), ovarian cancer, compared to malignancy cases in placebo patients, all of which were curable by surgical resection [basal cell carcinoma, cervical carcinoma in situ (2 cases)]. The incidence of malignancies in United States MAVENCLAD clinical study patients was higher than the rest of the world [4 events in 189 patient-years (2.21 events per 100 patient-years) compared to 0 events in United States placebo patients]; however, the United States results were based on a limited amount of patient data.

After the completion of 2 treatment courses, do not administer additional MAVENCLAD treatment during the next 2 years [see Dosage and Administration (2.2)]. In clinical studies, patients who received additional MAVENCLAD treatment within 2 years after the first 2 treatment courses had an increased incidence of malignancy [7 events in 790 patient-years (0.91 events per 100 patient-years) calculated from the start of cladribine treatment in Year 3]. The risk of malignancy with reinitiating MAVENCLAD more than 2 years after the completion of 2 treatment courses has not been studied.

MAVENCLAD is contraindicated in patients with current malignancy. In patients with prior malignancy or with increased risk of malignancy, evaluate the benefits and risks of the use of MAVENCLAD on an individual patient basis. Follow standard cancer screening guidelines in patients treated with MAVENCLAD.

5.2 Risk of Teratogenicity

MAVENCLAD may cause fetal harm when administered to pregnant women. Malformations and embryolethality occurred in animals [see Use in Specific Populations (8.1)]. Advise women of the potential risk to a fetus during MAVENCLAD dosing and for 6 months after the last dose in each treatment course.

In females of reproductive potential, pregnancy should be excluded before initiation of each treatment course of MAVENCLAD and prevented by the use of effective contraception during MAVENCLAD dosing and for at least 6 months after the last dose of each treatment course. Women who become pregnant during treatment with MAVENCLAD should discontinue treatment [see Use in Specific Populations (8.1, 8.3)]. MAVENCLAD is contraindicated for use in pregnant women and in women and men of reproductive potential who do not plan to use effective contraception.

5.3 Lymphopenia

MAVENCLAD causes a dose-dependent reduction in lymphocyte count. In clinical studies, 87% of MAVENCLAD-treated patients experienced lymphopenia. The lowest absolute lymphocyte counts occurred approximately 2 to 3 months after the start of each treatment course and were lower with each additional treatment course. In patients treated with a cumulative dose of MAVENCLAD 3.5 mg per kg over 2 courses as monotherapy, 26% and 1% had nadir absolute lymphocyte counts less than 500 and less than 200 cells per microliter, respectively. At the end of the second treatment course, 2% of clinical study patients had lymphocyte counts less than 500 cells per microliter; median time to recovery to at least 800 cells per microliter was approximately 28 weeks.

Additive hematological adverse reactions may be expected if MAVENCLAD is administered prior to or concomitantly with other drugs that affect the hematological profile [see Drug Interactions (7.3)]. The incidence of lymphopenia less than 500 cells per microliter was higher in patients who had used drugs to treat relapsing forms of MS prior to study entry (32.1%), compared to those with no prior use of these drugs (23.8%).

Obtain complete blood count (CBC) with differential including lymphocyte count prior to, during, and after treatment with MAVENCLAD. See Dosage and Administration (2.1, 2.5) and Warnings and Precautions (5.4) for timing of CBC measurements and additional instructions based on the patient's lymphocyte counts and clinical status (e.g., infections).

5.4 Infections

Serious, including life-threatening or fatal, bacterial, viral, parasitic, and fungal infections have been reported in patients receiving MAVENCLAD. MAVENCLAD reduces the body's immune defense, and an increased risk of infections has been observed in patients receiving MAVENCLAD.

Infections occurred in 49% of MAVENCLAD-treated patients compared to 44% of placebo patients in clinical studies; serious or severe infections occurred in 2.4% of MAVENCLAD-treated patients and 2.0% of placebo-treated patients. The most frequent serious infections in MAVENCLAD-treated patients included herpes zoster and pyelonephritis (see Herpes Virus Infections). Fungal infections were observed, including cases of coccidioidomycosis.

In the postmarketing setting, serious infections have been reported, including nocardiosis, varicella zoster, histoplasmosis, cryptococcosis, and toxoplasmosis. The majority of patients with these infections who had an available absolute lymphocyte count at the time of the event had concurrent lymphopenia, consistent with the mechanism of action of MAVENCLAD [see Warnings and Precautions (5.3)].

HIV infection, active tuberculosis, and active hepatitis must be excluded before initiation of each treatment course of MAVENCLAD [see Contraindications (4)].

Delay initiation of MAVENCLAD in patients with an acute infection until the infection is fully resolved or controlled.

Initiation of MAVENCLAD in patients currently receiving immunosuppressive or myelosuppressive therapy is not recommended [see Drug Interactions (7.1)]. Concomitant use of MAVENCLAD with these therapies could increase the risk of immunosuppression.

Tuberculosis

Three of 1,976 (0.2%) cladribine-treated patients in the clinical program developed tuberculosis. All three cases occurred in regions where tuberculosis is endemic. One case of tuberculosis was fatal, and two cases resolved with treatment.

Perform tuberculosis screening prior to initiation of the first and second treatment course of MAVENCLAD. Latent tuberculosis infections may be activated with use of MAVENCLAD. In patients with tuberculosis infection, delay initiation of MAVENCLAD until the infection has been adequately treated.

Hepatitis

One clinical study patient died from fulminant hepatitis B infection. Perform screening for hepatitis B and C prior to initiation of the first and second treatment course of MAVENCLAD. Latent hepatitis infections may be activated with use of MAVENCLAD. Patients who are carriers of hepatitis B or C virus may be at risk of irreversible liver damage caused by virus reactivation. In patients with hepatitis infection, delay initiation of MAVENCLAD until the infection has been adequately treated.

Herpes Virus Infections

In controlled clinical studies, 6% of MAVENCLAD-treated patients developed a herpes viral infection compared to 2% of placebo patients. The most frequent types of herpes viral infections were herpes zoster infections (2.0% vs. 0.2%) and oral herpes (2.6% vs. 1.2%). Serious herpes zoster infections occurred in 0.2% of MAVENCLAD-treated patients.

Vaccination of patients who are seronegative for varicella zoster virus is recommended prior to initiation of MAVENCLAD. Administer live-attenuated or live vaccines at least 4 to 6 weeks prior to starting MAVENCLAD. Vaccination with zoster vaccine recombinant, adjuvanted is recommended for patients who are seropositive to VZV, either prior to or during MAVENCLAD treatment, including when their lymphocyte counts are less than or equal to 500 cells per microliter.

The incidence of herpes zoster was higher during the period of absolute lymphocyte count less than 500 cells per microliter, compared to the time when the patients were not experiencing this degree of lymphopenia. Administer anti-herpes prophylaxis in patients with lymphocyte counts less than 200 cells per microliter.

Patients with lymphocyte counts below 500 cells per microliter should be monitored for signs and symptoms suggestive of infections, including herpes infections. If such signs and symptoms occur, initiate treatment as clinically indicated. Consider interruption or delay of MAVENCLAD until resolution of the infection.

Progressive Multifocal Leukoencephalopathy

Progressive multifocal leukoencephalopathy (PML) is an opportunistic viral infection of the brain caused by the JC virus (JCV) that typically only occurs in patients who are immunocompromised, and that usually leads to death or severe disability. Typical symptoms associated with PML are diverse, progress over days to weeks, and include progressive weakness on one side of the body or clumsiness of limbs, disturbance of vision, and changes in thinking, memory, and orientation leading to confusion and personality changes.

No case of PML has been reported in clinical studies of cladribine in patients with multiple sclerosis. In patients treated with parenteral cladribine for oncologic indications, cases of PML have been reported in the postmarketing setting.

Obtain a baseline (within 3 months) magnetic resonance imaging (MRI) before initiating the first treatment course of MAVENCLAD. At the first sign or symptom suggestive of PML, withhold MAVENCLAD and perform an appropriate diagnostic evaluation. MRI findings may be apparent before clinical signs or symptoms.

Vaccinations

Administer all immunizations (except as noted for VZV) according to immunization guidelines prior to starting MAVENCLAD. Administer live-attenuated or live vaccines at least 4 to 6 weeks prior to starting MAVENCLAD, because of a risk of active vaccine infection (see Herpes Virus Infections). Avoid vaccination with live-attenuated or live vaccines during and after MAVENCLAD treatment while the patient's white blood cell counts are not within normal limits.

5.5 Hematologic Toxicity

In addition to lymphopenia [see Warnings and Precautions (5.3)], decreases in other blood cells and hematological parameters have been reported with MAVENCLAD in clinical studies. Mild to moderate decreases in neutrophil counts (cell count between 1,000 cells per microliter and < lower limit of normal (LLN)) were observed in 27% of MAVENCLAD-treated patients, compared to 13% of placebo patients whereas severe decreases in neutrophil counts (cell count below 1,000 cells per microliter) were observed in 3.6% of MAVENCLAD-treated patients, compared to 2.8% of placebo patients. Decreases in hemoglobin levels, in general mild to moderate (hemoglobin 8.0 g per dL to < LLN), were observed in 26% of MAVENCLAD-treated patients, compared to 19% of placebo patients. Decreases in platelet counts were generally mild (cell count 75,000 cells per microliter to < LLN) and were observed in 11% of MAVENCLAD- treated patients, compared to 4% of placebo patients.

In clinical studies at dosages similar to or higher than the approved MAVENCLAD dosage, serious cases of thrombocytopenia, neutropenia, and pancytopenia (some with documented bone marrow hypoplasia) requiring transfusion and granulocyte-colony stimulating factor treatment have been reported [see Warnings and Precautions (5.6) for information regarding graft-versus- host disease with blood transfusion].

Obtain complete blood count (CBC) with differential prior to, during, and after treatment with MAVENCLAD [see Dosage and Administration (2.1, 2.5)].

5.6 Graft-Versus-Host Disease With Blood Transfusion

Transfusion-associated graft-versus-host disease has been observed rarely after transfusion of nonirradiated blood in patients treated with cladribine for non-MS treatment indications.

In patients who require blood transfusion, irradiation of cellular blood components is recommended prior to administration to decrease the risk of transfusion-related graft-versus-host disease. Consultation with a hematologist is advised.

5.7 Liver Injury

Mavenclad can cause liver injury. In clinical studies, 0.3% of MAVENCLAD-treated patients had liver injury (serious or causing treatment discontinuation) considered related to treatment, compared to 0 placebo patients. Onset ranged from a few weeks to several months after initiation of treatment with MAVENCLAD. Signs and symptoms of liver injury, including elevation of serum aminotransferases to greater than 20-fold the upper limit of normal, were observed. These abnormalities resolved upon treatment discontinuation.

Clinically significant and life-threatening liver injury has been reported in patients treated with MAVENCLAD in the postmarketing setting. Patients with pre-existing liver disease and patients taking other hepatotoxic drugs may be at increased risk for developing liver injury when taking MAVENCLAD. Most reported cases of liver injury associated with MAVENCLAD occurred approximately 30 days after initiation (i.e., course 1, cycle 1) of treatment.

MAVENCLAD is not recommended in patients with moderate to severe hepatic impairment (Child-Pugh score greater than 6) [see Use in Specific Populations (8.7), Clinical Pharmacology (12.3)].

Obtain serum aminotransferase, alkaline phosphatase, and total bilirubin levels prior to each treatment cycle and course [see Dosage and Administration (2.1)]. If a patient develops clinical signs, including unexplained liver enzyme elevations, or symptoms suggestive of hepatic dysfunction (e.g., unexplained nausea, vomiting, abdominal pain, fatigue, anorexia, or jaundice and/or dark urine), promptly measure serum transaminases and total bilirubin and interrupt or discontinue treatment with MAVENCLAD, as appropriate.

5.8 Hypersensitivity

In clinical studies, 11% of MAVENCLAD-treated patients had hypersensitivity reactions, compared to 7% of placebo patients. Hypersensitivity reactions that were serious and/or led to discontinuation of MAVENCLAD (e.g., dermatitis, pruritus) occurred in 0.5% of 13 MAVENCLAD-treated patients, compared to 0.1% of placebo patients. One patient had a serious hypersensitivity reaction with rash, mucous membrane ulceration, throat swelling, vertigo, diplopia, and headache after the first dose of MAVENCLAD.

If a hypersensitivity reaction is suspected, discontinue MAVENCLAD therapy. Do not use MAVENCLAD in patients with a history of hypersensitivity to cladribine [see Contraindications (4)].

5.9 Cardiac Failure

In clinical studies, one MAVENCLAD-treated patient experienced life-threatening acute cardiac failure with myocarditis, which improved after approximately one week. Cases of cardiac failure have also been reported with parenteral cladribine used for treatment indications other than multiple sclerosis.

Instruct patients to seek medical advice if they experience symptoms of cardiac failure (e.g., shortness of breath, rapid or irregular heartbeat, swelling).

6 ADVERSE REACTIONS

The following serious adverse reactions and potential risks are discussed, or discussed in greater detail, in other sections of the labeling:

- Malignancies [see Warnings and Precautions (5.1)]
- Risk of Teratogenicity [see Warnings and Precautions (5.2)]
- Lymphopenia [see Warnings and Precautions (5.3)]
- Infections [see Warnings and Precautions (5.4)]
- Hematologic Toxicity [see Warnings and Precautions (5.5)]
- Graft-Versus-Host Disease With Blood Transfusion [see Warnings and Precautions(5.6)]
- Liver Injury [see Warnings and Precautions (5.7)]
- Hypersensitivity [see Warnings and Precautions (5.8)]
- Cardiac Failure [see Warnings and Precautions (5.9)]

6.1 Clinical Trials Experience

Because clinical studies are conducted under widely varying conditions, adverse reaction rates observed in the clinical trials of a drug cannot be directly compared to rates in the clinical studies of another drug and may not reflect the rates observed in practice.

In the clinical trial program of cladribine in MS, 1,976 patients received cladribine for a total of 9,509 patient years. The mean time on study including follow-up was approximately 4.8 years, and approximately 24% of cladribine-treated patients had approximately 8 years of time on study including follow-up. Of these, 923 patients aged 18 to 66 years received MAVENCLAD as monotherapy at a cumulative dose of 3.5 mg per kg.

Table 2 shows adverse reactions in Study 1 [see Clinical Studies (14)] with an incidence of at least 5% for MAVENCLAD and higher than placebo. The most common (> 20%) adverse reactions reported in Study 1 are upper respiratory tract infection, headache, and lymphopenia.

Table 2 Adverse Reactions in Study 1 with an Incidence of at Least 5% for MAVENCLAD and Higher than Placebo
 | MAVENCLAD (N=440) % | Placebo (N=435) %
Upper respiratory tract infection | 38 | 32
Headache | 25 | 19
Lymphopenia | 24 | 2
Nausea | 10 | 9
Back pain | 8 | 6
Arthralgia and arthritis | 7 | 5
Insomnia | 6 | 4
Bronchitis | 5 | 3
Hypertension | 5 | 3
Fever | 5 | 3
Depression | 5 | 3

Hypersensitivity

In clinical studies, 11% of MAVENCLAD patients had hypersensitivity adverse reactions, compared to 7% of placebo patients [see Warnings and Precautions (5.8)].

Alopecia

Alopecia occurred in 3% of MAVENCLAD-treated patients compared to 1% of placebo patients.

Myelodysplastic Syndrome

Cases of myelodysplastic syndrome have been reported in patients that had received parenteral cladribine at a higher dosage than that approved for MAVENCLAD. These cases occurred several years after treatment.

Herpes Meningoencephalitis

Fatal herpes meningoencephalitis occurred in one MAVENCLAD-treated patient, at a higher dosage and longer duration of therapy than the approved MAVENCLAD dosage and in combination with interferon beta-1a treatment.

Stevens-Johnson syndrome (SJS) and toxic epidermal necrolysis (TEN)

SJS and TEN are identified risks of parenteral cladribine for the treatment of oncologic indications.

Seizures

In clinical studies, serious events of seizure occurred in 0.3% of MAVENCLAD-treated patients compared to 0 placebo patients. Serious events included generalized tonic-clonic seizures and status epilepticus. It is unknown whether these events were related to the effects of multiple sclerosis alone, to MAVENCLAD, or to a combination of both.

6.2 Postmarketing Experience

The following adverse reactions have been identified during postapproval use of MAVENCLAD. Because these reactions are reported voluntarily from a population of uncertain size, it is not always possible to reliably estimate their frequency or establish a causal relationship to drug exposure.

Infections and Infestations: nocardiosis, varicella zoster, histoplasmosis, cryptococcosis, and toxoplasmosis [see Warnings and Precautions (5.4)]

Hepatobiliary Disorders: liver injury [see Warnings and Precautions (5.7)]

7 DRUG INTERACTIONS

Table 3 Drug Interactions with MAVENCLAD
7.1 Immunomodulatory, Immunosuppressive, or Myelosuppressive Drugs
Clinical Impact | Concomitant use of MAVENCLAD with immunomodulatory, immunosuppressive, or myelosuppressive drugs may increase the risk of adverse reactions because of the additive effects on the immune system [see Warnings and Precautions (5.4)].
Prevention or Management | Concomitant use with myelosuppressive or other immunosuppressive drugs is not recommended. Acute short-term therapy with corticosteroids can be administered. In patients who have previously been treated with immunomodulatory or immunosuppressive drugs, consider potential additive effect, the mode of action, and duration of effect of the other drugs prior to initiation of MAVENCLAD.
7.2 Interferon-Beta
Clinical Impact | Concomitant use of MAVENCLAD with interferon-beta did not change the exposure of cladribine to a clinically significant effect; however, lymphopenia risk may be increased [see Warnings and Precautions (5.3)].
Prevention or Management | Concomitant use is not recommended.
7.3 Hematotoxic Drugs
Clinical Impact | Concomitant use of MAVENCLAD with hematotoxic drugs may increase the risk of adverse reactions because of the additive hematological effects [see Warnings and Precautions (5.5)].
Prevention or Management | Monitor hematological parameters.
7.4 Antiviral and Antiretroviral Drugs
Clinical Impact | Compounds that require intracellular phosphorylation to become active (e.g., lamivudine, zalcitabine, ribavirin, stavudine, and zidovudine) could interfere with the intracellular phosphorylation and activity of cladribine.
Prevention or Management | Avoid concomitant use.
7.5 Potent ENT, CNT and BCRP Transporter Inhibitors
Clinical Impact | Cladribine is a substrate of breast cancer resistance protein (BCRP), equilibrative nucleoside (ENT1), and concentrative nucleoside (CNT3) transport proteins. The bioavailability, intracellular distribution, and renal elimination of cladribine may be altered by potent ENT1, CNT3, and BCRP transporter inhibitors.
Prevention or Management | Avoid co-administration of potent ENT1, CNT3, or BCRP transporter inhibitors (e.g., ritonavir, eltrombopag, curcumin, cyclosporine, dilazep, nifedipine, nimodipine, cilostazol, sulindac, dipyridamole, or reserpine) during the 4 to 5 day MAVENCLAD treatment cycles. If this is not possible, consider selection of alternative concomitant drugs with no or minimal ENT1, CNT3, or BCRP transporter inhibiting properties. If this is not possible, dose reduction to the minimum mandatory dose of drugs containing these compounds, separation in the timing of administration, and careful patient monitoring is recommended.
7.6 Potent BCRP and P-gp Transporter Inducers
Clinical Impact | Possible decrease in cladribine exposure if potent BCRP or P-gp transporter inducers are co-administered.
Prevention or Management | Consider a possible decrease in cladribine efficacy if potent BCRP (e.g., corticosteroids) or P-gp (e.g., rifampicin, St. John's Wort) transporter inducers are co-administered.

8 USE IN SPECIFIC POPULATIONS

8.1 Pregnancy

Risk Summary

MAVENCLAD is contraindicated in pregnant women and in females and males of reproductive potential who do not plan to use effective contraception. There are no adequate data on the developmental risk associated with use of MAVENCLAD in pregnant women. Cladribine was embryolethal when administered to pregnant mice and produced malformations in mice and rabbits [see Data]. The observed developmental effects are consistent with the effects of cladribine on DNA [see Contraindications (4) and Warnings and Precautions (5.2)].

In the U.S. general population, the estimated background risk of major birth defects and miscarriage in clinically recognized pregnancies is 2% to 4% and 15% to 20%, respectively. The background risk of major birth defects and miscarriage for the indicated population is unknown.

There is a pregnancy safety study that monitors the pregnancy and infant outcomes following exposure to cladribine. Physicians and patients are encouraged to report pregnancies of women with multiple sclerosis exposed to oral cladribine during pregnancy or within 6 months before conception as well as pregnancies fathered by men with multiple sclerosis who had taken oral cladribine within 6 months before conception by calling EMD Serono's Adverse Event reporting line at 1-800-283-8088 ext. 5563 or by faxing 1-781-681-2961.

Data

Animal Data

When cladribine was administered intravenously (0, 0.5, 1.5, or 3 mg/kg/day) to pregnant mice during the period of organogenesis, fetal growth retardation and malformations (including exencephaly and cleft palate) and embryofetal death were observed at the highest dose tested. An increase in skeletal variations was observed at all but the lowest dose tested. There was no evidence of maternal toxicity.

When cladribine was administered intravenously (0, 0.3, 1, and 3 mg/kg/day) to pregnant rabbits during the period of organogenesis, fetal growth retardation and a high incidence of craniofacial and limb malformations were observed at the highest dose tested, in the absence of maternal toxicity.

When cladribine was administered intravenously (0, 0.5, 1.5, or 3.0 mg/kg/day) to mice throughout pregnancy and lactation, skeletal anomalies and embryolethality were observed at all but the lowest dose tested.

8.2 Lactation

Risk Summary

MAVENCLAD is contraindicated in breastfeeding women because of the potential for serious adverse reactions in breastfed infants [see Contraindications (4) and Warnings and Precautions (5)]. Advise women not to breastfeed during dosing with MAVENCLAD and for 10 days after the last dose.

There are no data on the presence of cladribine in human milk, the effects on the breastfed infant, or the effects of the drug on milk production.

8.3 Females and Males of Reproductive Potential

Pregnancy Testing

In females of reproductive potential, pregnancy should be excluded before the initiation of each treatment course of MAVENCLAD [see Use in Specific Populations (8.1)].

Contraception

Females

Females of reproductive potential should prevent pregnancy by use of effective contraception during MAVENCLAD dosing and for at least 6 months after the last dose in each treatment course. Women who become pregnant during MAVENCLAD therapy should discontinue treatment [see Warnings and Precautions (5.2)].

Males

As cladribine interferes with DNA synthesis, adverse effects on human gametogenesis could be expected. Therefore, male patients of reproductive potential should take precautions to prevent pregnancy of their partner during MAVENCLAD dosing and for at least 6 months after the last dose in each treatment course [see Warnings and Precautions (5.2) and Nonclinical Toxicology (13.1)].

8.4 Pediatric Use

The safety and effectiveness in pediatric patients (below 18 years of age) have not been established. Use of MAVENCLAD is not recommended in pediatric patients because of the risk of malignancies [see Warnings and Precautions (5.1)].

8.5 Geriatric Use

Clinical studies with MAVENCLAD did not include sufficient numbers of patients aged 65 and over to determine whether they respond differently from younger patients. Other reported clinical experience has not identified differences in responses between the elderly and younger patients. Caution is recommended when MAVENCLAD is used in elderly patients, taking into account the potential greater frequency of decreased hepatic, renal, or cardiac function, concomitant diseases, and other drug therapy.

8.6 Patients with Renal Impairment

The concentration of cladribine is predicted to increase in patients with renal impairment [see Clinical Pharmacology (12.3)]. No dosage adjustment is recommended in patients with mild renal impairment (creatinine clearance 60 to 89 mL per minute). MAVENCLAD is not recommended in patients with moderate to severe renal impairment (creatinine clearance below 60 mL per minute) [see Clinical Pharmacology (12.3)].

8.7 Patients with Hepatic Impairment

The effect of hepatic impairment on the pharmacokinetics of cladribine is unknown [see Clinical Pharmacology (12.3)]. No dosage adjustment is recommended in patients with mild hepatic impairment. MAVENCLAD is not recommended in patients with moderate to severe hepatic impairment (Child-Pugh score greater than 6) [see Warnings and Precautions (5.7), Clinical Pharmacology (12.3)].

10 OVERDOSAGE

There is no experience with overdose of MAVENCLAD. Lymphopenia is known to be dose- dependent. Particularly close monitoring of hematological parameters is recommended in patients who have been exposed to an overdose of MAVENCLAD [see Warnings and Precautions (5.3, 5.5)].

There is no known specific antidote to an overdose of MAVENCLAD. Treatment consists of careful observation and initiation of appropriate supportive measures. Discontinuation of MAVENCLAD may need to be considered. Because of the rapid and extensive intracellular and tissue distribution, hemodialysis is unlikely to eliminate cladribine to a significant extent.

11 DESCRIPTION

MAVENCLAD contains the nucleoside metabolic inhibitor cladribine, which is a white or almost white, non-hydroscopic, crystalline powder with the molecular formula C10H12ClN5O3 and molecular weight 285.69. It differs in structure from the naturally occurring nucleoside, deoxyadenosine, by the substitution of chlorine for hydrogen in the 2-position of the purine ring. The chemical name of cladribine is 2-chloro-2'-deoxy-adenosine.

The structural formula isshown below:

Cladribine is stable at slightly basic and at neutral pH. The main degradation pathway is hydrolysis and at acidic pH significant decomposition occurs with time. The ionization behavior of the molecule over the pH range 0 to 12 is characterized by a single pKa of approximately 1.21.

MAVENCLAD is provided as 10 mg tablets for oral use. Each MAVENCLAD 10 mg tablet contains cladribine as an active ingredient and hydroxypropyl betadex, magnesium stearate, and sorbitol as inactive ingredients.

12 CLINICAL PHARMACOLOGY

12.1 Mechanism of Action

The mechanism by which cladribine exerts its therapeutic effects in patients with multiple sclerosis has not been fully elucidated but is thought to involve cytotoxic effects on B and T lymphocytes through impairment of DNA synthesis, resulting in depletion of lymphocytes.

12.2 Pharmacodynamics

MAVENCLAD causes a dose-dependent reduction in lymphocyte count. The lowest absolute lymphocyte counts occurred approximately 2 to 3 months after the start of each treatment cycle and were lower with each additional treatment cycle. At the end of Year 2, 2% of patients continued to have absolute lymphocyte counts less than 500 cells per microliter. The median time to recovery from lymphocyte counts less than 500 cells per microliter to at least 800 cells per microliter was approximately 28 weeks [see Warnings and Precautions (5.3)].

12.3 Pharmacokinetics

Cladribine is a prodrug that becomes active upon phosphorylation to its 2-chlorodeoxyadenosine triphosphate (Cd-ATP) metabolite.

The pharmacokinetic parameters presented below were assessed following oral administration of cladribine 10 mg, unless otherwise specified. The cladribine mean maximum concentration (Cmax) was in the range of 22 to 29 ng/ mL and corresponding mean AUC was in the range of 80 to 101 ng∙h/mL.

The Cmax and AUC of cladribine increased proportionally across a dose range from 3 to 20 mg.

No accumulation of cladribine concentration in plasma was observed after repeated dosing.

Absorption

The bioavailability of cladribine was approximately 40%. Following fasted administration of cladribine, the median time to maximum concentration (Tmax) was 0.5 h (range 0.5 to 1.5 hours).

Effect of Food

Following administration of cladribine with a high fat meal, the geometric mean Cmax decreased by 29% and AUC was unchanged. The Tmax was prolonged to 1.5 hours (range 1 to 3 hours). This difference is not expected to be clinically significant.

Distribution

Cladribine mean apparent volume of distribution ranges from 480 to 490 liters. The plasma protein binding of cladribine is 20% and is independent of concentration, in vitro.

Intracellular concentrations of cladribine and/or its metabolites in human lymphocytes were approximately 30 to 40 times extracellular, in vitro.

Cladribine has the potential to penetrate the blood brain barrier. A cerebrospinal fluid/plasma concentration ratio of approximately 0.25 was observed in cancer patients.

Elimination

Cladribine estimated terminal half-life is approximately 1 day. The intracellular half-life of the cladribine phosphorylated metabolites cladribine monophosphate (Cd-AMP) is 15 hours and Cd- ATP is 10 hours. Cladribine estimated median apparent renal clearance is 22.2 liter per hour and non-renal clearance is 23.4 liter per hour.

Metabolism

Cladribine is a prodrug that is phosphorylated to Cd-AMP by deoxycytidine kinase (and also by deoxyguanosine kinase in the mitochondria) in lymphocytes. Cd-AMP is further phosphorylated to cladribine diphosphate (Cd-ADP) and the active moiety Cd-ATP. The dephosphorylation and deactivation of Cd-AMP is catalyzed by cytoplasmic 5'-nucleotidase (5'-Ntase).

The metabolism of cladribine in whole blood has not been fully characterized. However, extensive whole blood and negligible hepatic enzyme metabolism was observed, in vitro.

Excretion

After administration of 10 mg oral cladribine in MS patients, 28.5 [20] (mean [SD]) percent of the dose was excreted unchanged via the renal route. Renal clearance exceeded the glomerular filtration rate, indicating active renal secretion of cladribine.

Specific Populations

No studies have been conducted to evaluate the pharmacokinetics of cladribine in elderly or in patients with renal or hepatic impairment.

There were no clinically significant differences in the pharmacokinetics of cladribine based on age (range 18 to 65 years) or gender. The effect of hepatic impairment on the pharmacokinetics of cladribine is unknown.

Patients with Renal Impairment

Renal clearance of cladribine was shown to be dependent on creatinine clearance (CLCR). No dedicated studies have been conducted in patients with renal impairment, however patients with mild renal impairment (CLCR of 60 mL to below 90 mL per minute) were included in Study 1. A pooled pharmacokinetic analysis estimated a decrease of 18% in total clearance in a typical subject with a CLCR of 65 mL per minute leading to an increase in cladribine exposure of 25%. Clinical experience in patients with moderate to severe renal impairment (i.e., CLCR below 60 mL per minute) is limited [see Use in Specific Populations (8.6)].

Drug Interaction Studies

Clinical Studies

No clinically significant differences in cladribine pharmacokinetics were observed when used concomitantly with pantoprazole or interferon beta-1a.

No clinically significant differences in ethinyl estradiol and levonorgestrel pharmacokinetics were observed when a combined oral hormonal contraceptive (containing 150 μg levonorgestrel and 30 μg ethinyl estradiol) was used concomitantly with cladribine.

In Vitro Studies

It has been reported that lamivudine can inhibit the phosphorylation of cladribine intracellularly. Potential competition for intracellular phosphorylation exists between cladribine and compounds that require intracellular phosphorylation to become active (e.g., lamivudine, zalcitabine, ribavirin, stavudine, and zidovudine).

Cytochrome P450 (CYP) Enzymes: Cladribine is not a substrate of cytochrome P450 enzymes and does not show significant potential to act as inhibitor of CYP1A2, CYP2B6, CYP2C8, CYP2C9, CYP2C19, CYP2D6, CYP2E1 and CYP3A4. Cladribine has no clinically meaningful inductive effect on CYP1A2, CYP2B6 and CYP3A4 enzymes.

Transporter Systems: Cladribine is a substrate of P-glycoprotein (P-gp), breast cancer resistance protein (BCRP), equilibrative nucleoside transporter 1 (ENT1) and concentrative nucleoside transporter 3 (CNT3). Inhibition of BCRP in the gastrointestinal tract may increase the oral bioavailability and systemic exposure of cladribine. Intracellular distribution and renal elimination of cladribine may be altered by potent ENT1, CNT3 transporter inhibitors.

12.6 Hydroxypropyl Betadex-Related Complex Formation

MAVENCLAD contains hydroxypropyl betadex that may be available for complex formation with the active ingredients of other drugs. Complex formation between free hydroxypropyl betadex, released from the cladribine tablet formulation, and concomitant ibuprofen, furosemide, and gabapentin was observed. Concomitant use with MAVENCLAD may increase the bioavailability of other drugs (especially agents with low solubility), which may increase the risk or severity of adverse reactions [see Dosage and Administration (2.4)].

13 NONCLINICAL TOXICOLOGY

13.1 Carcinogenesis, Mutagenesis, Impairment of Fertility

Carcinogenesis

In mice administered cladribine (0, 0.1, 1, or 10 mg/kg) by subcutaneous injection intermittently (7 daily doses followed by 21 days of non-dosing per cycle) for 22 months, an increase in Harderian gland tumors (adenoma) was observed at the highest dose tested.

Mutagenesis

Cladribine was negative for mutagenicity in in vitro (reverse mutation in bacteria, CHO/HGPRT mammalian cell) assays.

Cladribine was positive for clastogenicity in an in vitro mammalian cell assay, in the absence and presence of metabolic activation, and in an in vivo mouse micronucleus assay.

Impairment of Fertility

When cladribine (0, 1, 5, 10, or 30 mg/kg/day) was administered by subcutaneous injection to male mice prior to and during mating to untreated females, no effects on fertility were observed. However, an increase in non-motile sperm was observed at the highest dose tested. In female mice, administration of cladribine (0, 1, 2, 4, or 8 mg/kg/day) by subcutaneous injection prior to and during mating to untreated males and continuing to gestation day 6 caused an increase in embryolethality at the highest dose tested.

In monkeys administered cladribine (0, 0.15, 0.3, or 1.0 mg/kg) by subcutaneous injection intermittently (7 consecutive daily doses followed by 21 days of non-dosing per cycle) for one year, testicular degeneration was observed at the highest dose tested.

14 CLINICAL STUDIES

The efficacy of MAVENCLAD was demonstrated in a 96-week randomized, double-blind, placebo-controlled clinical study in patients with relapsing forms of MS (Study 1; NCT00213135).

Patients were required to have at least 1 relapse in the previous 12 months. The median age was 39 years (range 18 to 65) and the female-to-male ratio was approximately 2:1. The mean duration of MS prior to study enrollment was 8.7 years, and the median baseline neurological disability based on Kurtzke Expanded Disability Status Scale (EDSS) score across all treatment groups was 3.0. Over two thirds of the study patients were treatment-naive for drugs used to treat relapsing forms of MS.

1,326 patients were randomized to receive either placebo (n = 437), or a cumulative oral dosage of MAVENCLAD 3.5 mg per kg (n = 433) or 5.25 mg per kg body weight (n = 456) over the 96-week study period in 2 treatment courses. Patients randomized to the 3.5 mg per kg cumulative dose received a first treatment course at Weeks 1 and 5 of the first year and a second treatment course at Weeks 1 and 5 of the second year [see Dosage and Administration (2.2)]. Patients randomized to the 5.25 mg per kg cumulative dose received additional treatment at Weeks 9 and 13 of the first year. Higher cumulative doses did not add any clinically meaningful benefit, but were associated with a higher incidence in grade 3 lymphopenia or higher (44.9% in the 5.25 mg per kg group vs. 25.6% in the 3.5 mg per kg group). Ninety-two percent of patients treated with MAVENCLAD 3.5 mg per kg and 87% of patients receiving placebo completed the full 96 weeks of the study.

The primary outcome of Study 1 was the annualized relapse rate (ARR). Additional outcome measures included the proportion of patients with confirmed disability progression, the time to first qualifying relapse, the mean number of MRI T1 Gadolinium-enhancing (Gd+) lesions, and new or enlarging MRI T2 hyperintense lesions. Disability progression was measured in terms of a 3-month sustained change in EDSS score of at least one point, if baseline EDSS score was between 0.5 and 4.5 inclusively, or at least 1.5 points if the baseline EDSS score was 0, or at least 0.5 point if the baseline EDSS score was at least 5, over a period of at least 3 months.

MAVENCLAD 3.5 mg per kg significantly lowered the annualized relapse rate. The results from Study 1 are presented in Table 4.

Table 4 Clinical Outcomes in Study 1 (96 Weeks) - Primary and Secondary Endpoints
Endpoints | MAVENCLAD Cumulative Dose 3.5 mg per kg | Placebo
Endpoints | (n = 433) | (n = 437)
Clinical Endpoints
Annualized relapse rate (ARR) | 0.14 [p < 0.001 compared to placebo] | 0.33
Relative reduction in ARR | 58%
Proportion of patients without relapse | 81% [nominal p < 0.05 compared to placebo] | 63%
Time to 3-month confirmed EDSS progression, HR | 0.67
Proportion of patients with 3-month EDSS progression | 13% | 19%
MRI Endpoints
Median Number of Active T1 Gd+ Lesions | 0 | 0.33
Median Number of Active T2 Lesions | 0 | 0.67
HR: Hazard Ratio

15 REFERENCES

1 "OSHA Hazardous Drugs". OSHA. http://www.osha.gov/SLTC/hazardousdrugs/index.html.

16 HOW SUPPLIED/STORAGE AND HANDLING

16.1 How Supplied

MAVENCLAD tablets, 10 mg, are uncoated, white, round, biconvex, and engraved with a "C" on one side and "10" on the other side. Each tablet is packaged in a child-resistant day pack containing one or two tablets in a blister card.

Dispense one box for each treatment cycle with a Medication Guide [see Dosage and Administration (2.2)].

Presentations

NDC 44087-4000-4 | Box of 4 tablets: Four day packs each containing one tablet.
NDC 44087-4000-5 | Box of 5 tablets: Five day packs each containing one tablet.
NDC 44087-4000-6 | Box of 6 tablets: One day pack containing two tablets. Four day packs each containing one tablet.
NDC 44087-4000-7 | Box of 7 tablets: Two day packs each containing two tablets. Three day packs each containing one tablet.
NDC 44087-4000-8 | Box of 8 tablets: Three day packs each containing two tablets. Two day packs each containing one tablet.
NDC 44087-4000-9 | Box of 9 tablets: Four day packs each containing two tablets. One day pack containing one tablet.
NDC 44087-4000-0 | Box of 10 tablets: Five day packs each containing two tablets.

16.2 Storage and Handling

Store at controlled room temperature, 20°C to 25°C (68°F to 77°F); excursions permitted to 15°C to 30°C (59°F to 86°F) [see USP Controlled Room Temperature]. Store in original package in order to protect from moisture.

MAVENCLAD is a cytotoxic drug. Follow applicable special handling and disposal procedures [see References (15)].^1

17 PATIENT COUNSELING INFORMATION

Advise the patient to read the FDA-approved patient labeling (Medication Guide).

Malignancies

Inform patients that MAVENCLAD may increase their risk of malignancies. Instruct patients to follow standard cancer screening guidelines [see Dosage and Administration (2) and Warnings and Precautions (5.1)].

Risk of Teratogenicity

Inform patients that MAVENCLAD may cause fetal harm. Discuss with women of childbearing age whether they are pregnant, might be pregnant, or are trying to become pregnant. Before initiating each treatment course, inform patients about the potential risk to the fetus, if female patients or partners of male patients get pregnant during MAVENCLAD dosing or within 6 months after the last dose in each treatment course [see Warnings and Precautions (5.2) and Use in Specific Populations (8.1, 8.3)].

Instruct female patients of childbearing potential to use effective contraception during MAVENCLAD dosing and for at least 6 months after the last dose in each treatment course to avoid pregnancy.

Instruct male patients to take precautions to prevent pregnancy of their partner during MAVENCLAD dosing and for at least 6 months after the last dose in each treatment course.

Advise patients that female patients or partners of male patients who get pregnant immediately inform their healthcare provider.

Advise patients that there is a pregnancy safety study that monitors the pregnancy outcomes in women exposed to cladribine during pregnancy or within 6 months before conception, as well as pregnancies fathered by men exposed to cladribine within 6 months before conception, and they can report the pregnancy by calling EMD Serono's Adverse Event reporting line at 1-800-283-8088 ext. 5563 or by faxing 1-781-681-2961 [see Use in Specific Populations (8.1)].

Lactation

Inform women that they cannot breastfeed on a MAVENCLAD treatment day and for 10 days after the last dose [see Use in Specific Populations (8.2)].

Lymphopenia and Other Hematologic Toxicity

Inform patients that MAVENCLAD decreases lymphocyte counts and may also decrease counts of other blood cells. A blood test should be obtained before starting a treatment course, 2 and 6 months after start of treatment in each treatment course, periodically thereafter, and when clinically needed. Advise patients to keep all appointments for lymphocyte monitoring during and after MAVENCLAD treatment [see Dosage and Administration (2.5) and Warnings and Precautions (5.3, 5.5)].

Infections

Inform patients that infections, some of which were serious, have been reported in patients receiving MAVENCLAD. Instruct patients to notify their healthcare provider promptly if fever or other signs of infection such as aching, painful muscles, headache, generally feeling unwell or loss of appetite occur while on therapy orafter a course of treatment [see Warnings and Precautions (5.4)].

Advise patients that PML has happened with parenteral cladribine used in oncologic indications. Inform the patient that PML is characterized by a progression of deficits and usually leads to death or severe disability over weeks or months. Instruct the patient of the importance of contacting their doctor if they develop any symptoms suggestive of PML. Inform the patient that typical symptoms associated with PML are diverse, progress over days to weeks, and include progressive weakness on one side of the body or clumsiness of limbs, disturbance of vision, and changes in thinking, memory, and orientation leading to confusion and personality changes [see Warnings and Precautions (5.4)].

Advise patients that some vaccines containing live virus (live attenuated vaccines) should be avoided during and after treatment with MAVENCLAD. Advise patients to complete any live or live-attenuated vaccinations at least 4 to 6 weeks prior to initiation of MAVENCLAD. Instruct patients to contact their healthcare provider prior to receiving any vaccinations.

Liver Injury

Inform patients that liver injury has been reported in patients receiving MAVENCLAD. Instruct patients treated with MAVENCLAD to report promptly any symptoms that may indicate liver injury, including fatigue, anorexia, right upper abdominal discomfort, dark urine, or jaundice. A blood test should be obtained prior to each treatment cycle and course with MAVENCLAD and as clinically indicated thereafter [see Warnings and Precautions (5.7)].

Hypersensitivity

Advise patients to seek immediate medical attention if they experience any symptoms of serious or severe hypersensitivity reactions, including skin reactions [see Warnings and Precautions (5.8)].

Cardiac Failure

Advise patients that MAVENCLAD may cause cardiac failure. Instruct patients to seek medical advice if they experience symptoms of cardiac failure (e.g., shortness of breath, rapid or irregular heartbeat, swelling) [see Warnings and Precautions (5.9)].

Treatment Handling and Administration

Instruct patients that MAVENCLAD is a cytotoxic drug and to use care when handling MAVENCLAD tablets, limit direct skin contact with the tablets, and wash exposed areas thoroughly. Advise patients to keep the tablets in the original package until just prior to each scheduled dose and consult their pharmacist on the proper disposal of unused tablets [see Dosage and Administration (2.4) and How Supplied/Storage and Handling (16.2)].

Distributed by:
EMD Serono, Inc.Boston, MA 02210

MAVENCLAD is a registered trademark of Merck KGaA, Darmstadt, Germany.

MEDICATION GUIDE
MAVENCLAD® (MAY-ven-klad)
(cladribine)
tablets, for oral use

What is the most important information I should know about MAVENCLAD?

MAVENCLAD can cause serious side effects, including:

- Risk of cancer (malignancies). Treatment with MAVENCLAD may increase your risk of developing cancer. Talk to your healthcare provider about your risk of developing cancer if you receive MAVENCLAD. You should follow your healthcare provider's instructions about screening for cancer.
- MAVENCLAD may cause birth defects if used during pregnancy. Women must not be pregnant when they start treatment with MAVENCLAD or become pregnant during MAVENCLAD dosing and within 6 months after the last dose of each yearly treatment course. Stop your treatment with MAVENCLAD and call your healthcare provider right away if you become pregnant during treatment with MAVENCLAD.
  - For women who are able to become pregnant:
    - Your healthcare provider should order a pregnancy test for you before you begin your first and second yearly treatment course of MAVENCLAD to make sure that you are not pregnant. Your healthcare provider will decide when to do the test.
    - Use effective birth control (contraception) on the days on which you take MAVENCLAD and for at least 6 months after the last dose of each yearly treatment course.
      Ask your healthcare provider which contraception method is right for you.
  - For men with female partners who are able to become pregnant:
    - Use effective birth control (contraception) during the days on which you take MAVENCLAD and for at least 6 months after the last dose of each yearly treatment course.
- MAVENCLAD Pregnancy Safety Study
  - For women treated with MAVENCLAD: if you become pregnant while taking MAVENCLAD or during the 6 months after your last dose.
  - For men treated with MAVENCLAD with a female partner: if your partner becomes pregnant while you are taking MAVENCLAD or during the 6 months after your last dose.
    The purpose of this program is to assess the effect of MAVENCLAD exposure on pregnancy and infant outcomes. Either you or your healthcare provider can report your information by calling 1-800-283-8088 ext. 5563 or by fax 1-781-681-2961.

What is MAVENCLAD?

MAVENCLAD is a prescription medicine used to treat relapsing forms of multiple sclerosis (MS), to include relapsing-remitting disease and active secondary progressive disease, in adults. Because of its risks, MAVENCLAD is generally used in people who have tried another MS medicine that they could not tolerate or that has not worked well enough.

MAVENCLAD is not recommended for use in people with clinically isolated syndrome (CIS).

It is not known if MAVENCLAD is safe and effective in children under 18 years of age.

Do not take MAVENCLAD if you:

- have cancer (malignancy).
- are pregnant, plan to become pregnant, or are a woman of childbearing age or a man able to father a child and you are not using birth control. See "What is the most important information I should know about MAVENCLAD?"
- are human immunodeficiency virus (HIV) positive.
- have active infections, including tuberculosis (TB), hepatitis B or C.
- are allergic to cladribine.
- are breastfeeding. See "Before you take MAVENCLAD, tell your healthcare provider about all of your medical conditions, including if you:"

Before you take MAVENCLAD, tell your healthcare provider about all of your medical conditions, including if you:

- think you have an infection.
- have heart failure.
- have liver or kidney problems.
- have taken, take, or plan to take medicines that affect your immune system or your blood cells, or other treatments for MS. Certain medicines can increase your risk of getting an infection.
- have had a recent vaccination or are scheduled to receive any vaccinations. You should not receive live or live-attenuated vaccines within the 4 to 6 weeks before you start your treatment with MAVENCLAD. You should not receive these types of vaccines during your treatment with MAVENCLAD and until your healthcare provider tells you that your immune system is no longer weakened.
- have or have had cancer.
- are breastfeeding or plan to breastfeed. It is not known if MAVENCLAD passes into your breast milk. Do not breastfeed on the days on which you take MAVENCLAD, and for 10 days after the last dose. See "Do not take MAVENCLAD if you:"

Tell your healthcare provider about all the medicines you take, including prescription and over-the-counter medicines, vitamins, and herbal supplements.

How should I take MAVENCLAD?

- MAVENCLAD is given as two yearly treatment courses.
- Each yearly treatment course consists of 2 treatment weeks (also called cycles) that will be about a month apart. Your healthcare provider will tell you when you have to start your treatment weeks and how many tablets per week you need, depending on your weight. Each treatment week is 4 or 5 days.
- Your pharmacist will dispense a carton of MAVENCLAD for each treatment week. The prescribed number of tablets per day are provided in child resistant day packs.
- Take MAVENCLAD exactly as your healthcare provider tells you. Do not change your dose or stop taking MAVENCLAD unless your healthcare provider tells you to.
- Take MAVENCLAD with water and swallow whole without chewing. MAVENCLAD can be taken with or without food.
- Swallow MAVENCLAD right away after opening the blister pack.
- Your hands must be dry when handling MAVENCLAD and washed well with water afterwards.
- Limit contact with your skin. Avoid touching your nose, eyes and other parts of the body. If you get MAVENCLAD on your skin or on any surface, wash it right away with water.
- Take MAVENCLAD at least 3 hours apart from other medicines taken by mouth during the 4- to 5-day MAVENCLAD treatment week.
- If you miss a dose, take it as soon as you remember on the same day. If the whole day passes before you remember, take your missed dose the next day. Do not take 2 doses at the same time. Instead, you will extend the number of days in that treatment week.

Your healthcare provider will continue to monitor your health during the 2 yearly treatment courses, and for at least another 2 years during which you do not need to take MAVENCLAD. It is not known if MAVENCLAD is safe and effective in people who restart MAVENCLAD treatment more than 2 years after completing 2 yearly treatment courses.

What are the possible side effects of MAVENCLAD?

MAVENCLAD can cause serious side effects, including:

- See "What is the most important information I should know about MAVENCLAD?"
- low blood cell counts. Low blood cell counts have happened and can increase your risk of infections during your treatment with MAVENCLAD. Your healthcare provider will do blood tests before you start treatment with MAVENCLAD, during your treatment with MAVENCLAD, and afterward, as needed.
- serious infections such as:
  - Infections caused by bacteria, viruses, parasites, or fungi that may be life-threatening or cause death.
  - TB, hepatitis B or C, and shingles (herpes zoster). Fatal cases of TB and hepatitis have happened with cladribine during clinical studies. Tell your healthcare provider right away if you get any symptoms of the following infection related problems or if any of the symptoms get worse, including:

- fever
- aching painful muscles
- headache
- feeling of being generally unwell

- loss of appetite
- burning, tingling, numbness or itchiness of the skin in the affected area
- skin blotches, blistered rash and severe pain

- progressive multifocal leukoencephalopathy (PML). PML is a rare brain infection that usually leads to death or severe disability. Although PML has not been seen in MS patients taking MAVENCLAD, it may happen in people with weakened immune systems. Symptoms of PML get worse over days to weeks. Call your healthcare provider right away if you have any new or worsening neurologic signs or symptoms of PML, that have lasted several days, including:

- weakness on 1 side of your body
- loss of coordination in your arms and legs
- decreased strength
- problems with balance

  - changes in your vision
  - changes in your thinking or memory
  - confusion
  - changes in your personality

- liver problems. MAVENCLAD may cause liver damage. Your risk of developing serious liver problems may be higher if you already have liver problems or take other medicines that also affect your liver. Your healthcare provider should do blood tests to check your liver:
  - before you start taking MAVENCLAD
  - before each course and cycle of MAVENCLAD treatment
  Call your healthcare provider right away if you have any of the following symptoms of liver problems:

- nausea
- vomiting
- stomach pain
- tiredness

- loss of appetite
- your skin or the whites or your eyes turn yellow
- dark urine

- allergic reactions (hypersensitivities). MAVENCLAD can cause serious allergic reactions. Stop your treatment with MAVENCLAD and go to the closest emergency room for medical help right away if you have any signs or symptoms of allergic reactions. Symptoms of an allergic reaction may include: skin rash, swelling or itching of the face, lips, tongue or throat, or trouble breathing.
- heart failure. MAVENCLAD may cause heart failure, which means your heart may not pump as well as it should. Call your healthcare provider or go to the closest emergency room for medical help right away if you have any signs or symptoms such as shortness of breath, a fast or irregular heartbeat, or unusual swelling in your body.

Your healthcare provider may delay or completely stop treatment with MAVENCLAD if you have severe side effects.

The most common side effects of MAVENCLAD include:

- upper respiratory infection

- headache

- low white blood cell counts

These are not all the possible side effects of MAVENCLAD. Call your doctor for medical advice about side effects. You may report side effects to FDA at 1-800-FDA-1088.

How should I store MAVENCLAD?

- MAVENCLAD comes in a child resistant package.
- Store MAVENCLAD at room temperature between 68°F and 77°F (20°C and 25°C).
- Store MAVENCLAD in the original package to protect from moisture.
- Ask your healthcare provider or pharmacist about how to safely throw away any unused or expired MAVENCLAD tablets and packaging.

Keep MAVENCLAD and all medicines out of the reach of children.

General information about the safe and effective use of MAVENCLAD:

Medicines are sometimes prescribed for purposes other than those listed in a Medication Guide. Do not use MAVENCLAD for a condition for which it was not prescribed. Do not give MAVENCLAD to other people, even if they have the same symptoms that you have. It may harm them. You can ask your healthcare provider for information about MAVENCLAD that is written for health professionals.

What are the ingredients in MAVENCLAD?

Active ingredient: cladribine

Inactive ingredients: hydroxypropyl betadex, magnesium stearate, and sorbitol.

Distributed by: EMD Serono, Inc., Boston, MA 02210
MAVENCLAD is a registered trademark of Merck KGaA, Darmstadt, Germany.
For more information, call toll-free1-877-447-3243 or go to www.mavenclad.com

This Medication Guide has been approved by the U.S. Food and Drug Administration.

Revised: 01/2025

PRINCIPAL DISPLAY PANEL - 4 Tablet Blister Pack Carton

NDC 44087-4000-4

MAVENCLAD®
(cladribine) tablets
10 mg per tablet

Contents:
4 tablets: Four child-resistant day packs each
containing one 10 mg tablet in blister card.

Dosage and Administration:
Based on body weight. For oral administration.
See enclosed Prescribing Information and Medication
Guide.

Separate ingestion of other oral medicines by at
least 3 hours before and after taking MAVENCLAD.

Cytotoxic Agent:
Handle tablets as directed.

Dispense with enclosed Medication Guide.

Rx Only

4 Tablets

EMD
SERONO